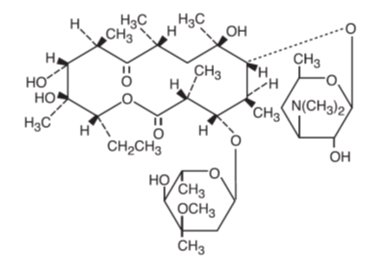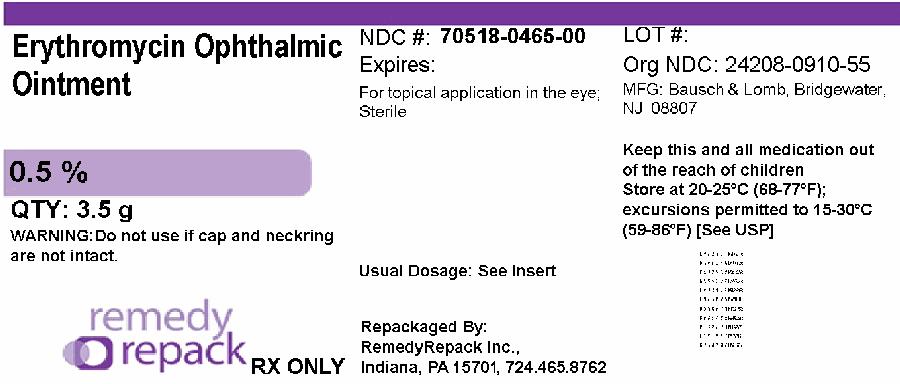 DRUG LABEL: Erythromycin
NDC: 70518-0465 | Form: OINTMENT
Manufacturer: REMEDYREPACK INC.
Category: prescription | Type: HUMAN PRESCRIPTION DRUG LABEL
Date: 20260105

ACTIVE INGREDIENTS: ERYTHROMYCIN 5 mg/1 g
INACTIVE INGREDIENTS: PETROLATUM; MINERAL OIL

Erythromycin
Ophthalmic
Ointment
USP
0.5%
(Sterile)
Rx only

DESCRIPTION

Erythromycin ophthalmic ointment, USP belongs to the macrolide group of antibiotics. The sterile ophthalmic ointment flows freely over the conjunctiva. Erythromycin base, as crystals or powder, is slightly soluble in water, moderately soluble in ether, and readily soluble in alcohol or chloroform. Erythromycin is an antibiotic produced from a strain of Streptomyces erythraeus. It is basic and readily forms a salt when combined with an acid. It has the following structural formula:

Molecular Formula: C37H67NO13 | Mol. Wt. 733.94

Chemical Name: ((3R●,4S●,5S●,6R●,7R●,9R●,11R●,12R●,13S●,14R●)-4-[(2,6-dideoxy-3- C-methyl-3- 0-methyl-α-L- ribo-hexopyranosyl)oxy]-14-ethyl-7,12,13-trihydroxy-3,5,7,9,11,13-hexamethyl-6-[[3,4,6-trideoxy-3-(dimethylamino)- β-D- xylo-hexopyranosyl]oxy]oxacyclotetradecane-2,10-dione)

Each gram contains: Active: erythromycin USP, 5 mg (0.5%); Inactives: mineral oil and white petrolatum.

CLINICAL PHARMACOLOGY

Microbiology

Erythromycin inhibits protein synthesis without affecting nucleic acid synthesis. Erythromycin is usually active against the following organisms in vitro and in clinical infections: Streptococcus pyogenes(group A β-hemolytic), Alpha-hemolytic streptococci (viridans group); Staphylococcus aureus,including penicillinase-producing strains (methicillin-resistant staphylococci are uniformly resistant to erythromycin); Streptococcus pneumoniae; Mycoplasma pneumoniae(Eaton Agent, PPLO); Haemophilus influenzae(not all strains of this organism are susceptible at the erythromycin concentrations ordinarily achieved); Treponema pallidum; Corynebacterium diphtheriae; Neisseria gonorrhoeae; Chlamydia trachomatis.

INDICATIONS AND USAGE

For the treatment of superficial ocular infections involving the conjunctiva and/or cornea caused by organisms susceptible to erythromycin.

For prophylaxis of ophthalmia neonatorum due to N. gonorrhoeaeor C. trachomatis.

The effectiveness of erythromycin in the prevention of ophthalmia caused by penicillinase-producing N. gonorrhoeaeis not established.

For infants born to mothers with clinically apparent gonorrhea, intravenous or intramuscular injections of aqueous crystalline penicillin G should be given: a single dose of 50,000 units for term infants or 20,000 units for infants of low birth weight. Topical prophylaxis alone is inadequate for these infants.

CONTRAINDICATIONS

This drug is contraindicated in patients with a history of hypersensitivity to erythromycin.

PRECAUTIONS

General

The use of antimicrobial agents may be associated with the overgrowth of non-susceptible organisms including fungi; in such a case, antibiotic administration should be stopped and appropriate measures taken.

Information for Patients:Avoid contaminating the applicator tip with material from the eye, fingers, or other source.

Carcinogenesis, Mutagenesis, Impairment of Fertility:Two year oral studies conducted in rats with erythromycin did not provide evidence of tumorigenicity. Mutagenicity studies have not been conducted.

No evidence of impaired fertility that appeared related to erythromycin was reported in animal studies.

Pregnancy:Reproduction studies have been performed in rats, mice, and rabbits using erythromycin and its various salts and esters, at doses that were several multiples of the usual human dose. No evidence of harm to the fetus that appeared related to erythromycin was reported in these studies. There are, however, no adequate and well-controlled studies in pregnant women. Because animal reproductive studies are not always predictive of human response, the erythromycins should be used during pregnancy only if clearly needed.

Nursing Mothers:Caution should be exercised when erythromycin is administered to a nursing woman.

Pediatric Use:See INDICATIONS AND USAGEand DOSAGE AND ADMINISTRATION.

ADVERSE REACTIONS

The most frequently reported adverse reactions are minor ocular irritations, redness, and hypersensitivity reactions.

To report SUSPECTED ADVERSE REACTIONS, contact Bausch & Lomb Incorporated at 1-800-553-5340 or FDA at 1-800-FDA-1088 or www.fda.gov/medwatch.

DOSAGE AND ADMINISTRATION

In the treatment of superficial ocular infections, erythromycin ophthalmic ointment approximately 1 cm in length should be applied directly to the infected eye(s) up to six times daily, depending on the severity of the infection.

For prophylaxis of neonatal gonococcal or chlamydial ophthalmia, a ribbon of ointment approximately 1 cm in length should be instilled into each lower conjunctival sac. The ointment should not be flushed from the eye following instillation. A new tube should be used for each infant.

HOW SUPPLIED

Erythromycin ophthalmic ointment USP, 0.5% is available in the following sizes:

3.5 g (1/8 oz) in a tamper-resistant tube

NDC: 70518-0465-00

PACKAGING: 1 in 1 CARTON, 3.50 g in 1 TUBE TYPE 0

Storage:Store between 15°C to 25°C (59°F to 77°F).

Keep out of reach of children.

Repackaged and Distributed By:

Remedy Repack, Inc.

625 Kolter Dr. Suite #4 Indiana, PA 1-724-465-8762

PACKAGE LABEL

DRUG: Erythromycin

GENERIC: Erythromycin

DOSAGE: OINTMENT

ADMINSTRATION: OPHTHALMIC

NDC: 70518-0465-0

PACKAGING: 3.5 g in 1 TUBE

OUTER PACKAGING: 1 in 1 CARTON

ACTIVE INGREDIENT(S):

- ERYTHROMYCIN 5mg in 1g

INACTIVE INGREDIENT(S):

- PETROLATUM
- MINERAL OIL